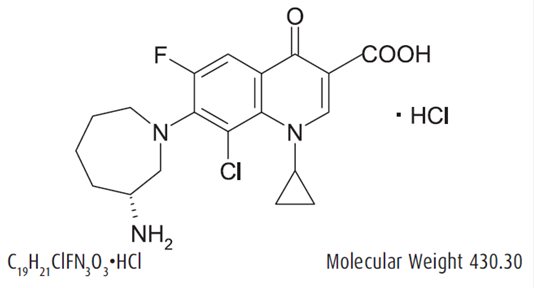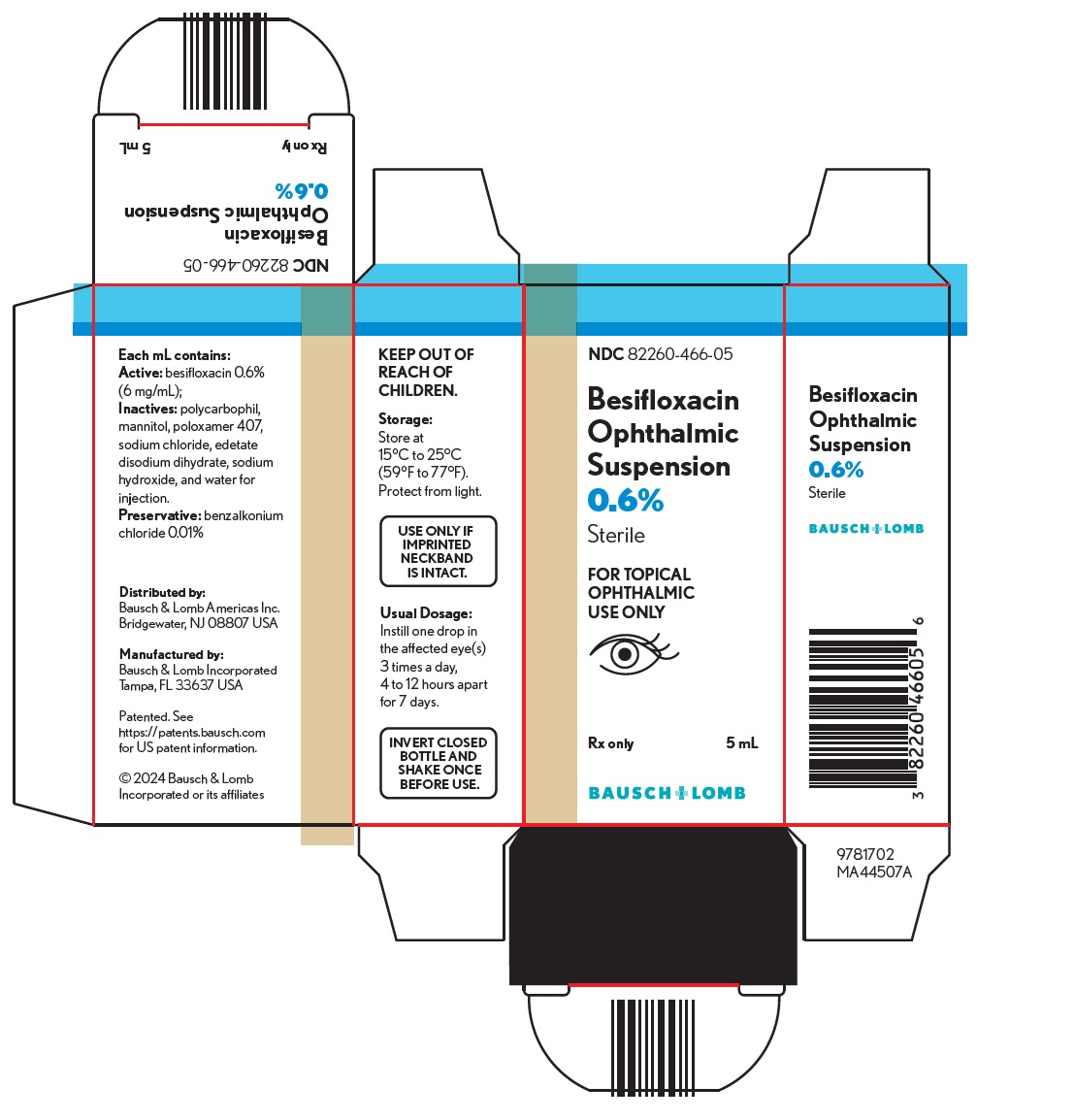 DRUG LABEL: Besivance
NDC: 82260-466 | Form: SUSPENSION
Manufacturer: Bausch & Lomb Americas Inc.
Category: prescription | Type: HUMAN PRESCRIPTION DRUG LABEL
Date: 20260112

ACTIVE INGREDIENTS: BESIFLOXACIN 6 mg/1 mL
INACTIVE INGREDIENTS: BENZALKONIUM CHLORIDE; POLYCARBOPHIL; MANNITOL; POLOXAMER 407; SODIUM CHLORIDE; EDETATE DISODIUM; SODIUM HYDROXIDE; WATER

HIGHLIGHTS OF PRESCRIBING INFORMATION

These highlights do not include all the information needed to use BESIFLOXACIN OPHTHALMIC SUSPENSION safely and effectively. See full prescribing information for BESIFLOXACIN OPHTHALMIC SUSPENSION.
BESIFLOXACIN OPHTHALMIC SUSPENSION, for topical ophthalmic use
Initial U.S. Approval: 2009

1 INDICATIONS AND USAGE

Besifloxacin ophthalmic suspension 0.6% is a quinolone antimicrobial indicated for the treatment of bacterial conjunctivitis caused by susceptible isolates of the following bacteria:

Aerococcus viridans*,CDC coryneform group G, Corynebacterium pseudodiphtheriticum*, Corynebacterium striatum*, Haemophilus influenzae, Moraxella catarrhalis*, Moraxella lacunata*, Pseudomonas aeruginosa*, Staphylococcus aureus, Staphylococcus epidermidis, Staphylococcus hominis*, Staphylococcus lugdunensis*, Staphylococcus warneri*, Streptococcus mitisgroup , Streptococcus oralis, Streptococcus pneumoniae, Streptococcus salivarius*

*Efficacy for this organism was studied in fewer than 10 infections. (1)

2 DOSAGE AND ADMINISTRATION

Instill one drop in the affected eye(s) 3 times a day, 4 to 12 hours apart for 7 days. (2)

3 DOSAGE FORMS AND STRENGTHS

Ophthalmic suspension: besifloxacin 6 mg/mL (0.6%) (3)

4 CONTRAINDICATIONS

None. (4)

5 WARNINGS AND PRECAUTIONS

- Not for Injection into the Eye (5.1)
- Growth of Resistant Organisms with Prolonged Use (5.2)
- Avoidance of Contact Lenses: Patients should not wear contact lenses if they have signs or symptoms of bacterial conjunctivitis or during the course of therapy with besifloxacin ophthalmic suspension. (5.3)

6 ADVERSE REACTIONS

The most common adverse reaction reported in 2% of patients treated with besifloxacin ophthalmic suspension was conjunctival redness. (6)

To report SUSPECTED ADVERSE REACTIONS, contact Bausch & Lomb Incorporated at 1-800-553-5340 or FDA at 1-800-FDA-1088 or www.fda.gov/medwatch.

FULL PRESCRIBING INFORMATION

1 INDICATIONS AND USAGE

Besifloxacin ophthalmic suspension 0.6% is indicated for the treatment of bacterial conjunctivitis caused by susceptible isolates of the following bacteria:

1. Aerococcus viridans*
2. CDC coryneform group G
3. Corynebacterium pseudodiphtheriticum*
4. Corynebacterium striatum*
5. Haemophilus influenzae
6. Moraxella catarrhalis*
7. Moraxella lacunata*
8. Pseudomonas aeruginosa*
9. Staphylococcus aureus
10. Staphylococcus epidermidis
11. Staphylococcus hominis*
12. Staphylococcus lugdunensis*
13. Staphylococcus warneri*
14. Streptococcus mitisgroup
15. Streptococcus oralis
16. Streptococcus pneumoniae

Streptococcus salivarius*

1. *Efficacy for this organism was studied in fewer than 10 infections.

2 DOSAGE AND ADMINISTRATION

Invert closed bottle and shake once before use. Instill one drop in the affected eye(s) 3 times a day, 4 to 12 hours apart for 7 days.

3 DOSAGE FORMS AND STRENGTHS

Ophthalmic suspension containing 6 mg/mL (0.6%) of besifloxacin.

4 CONTRAINDICATIONS

None.

5 WARNINGS AND PRECAUTIONS

5.2 Growth of Resistant Organisms with Prolonged Use

As with other anti-infectives, prolonged use of besifloxacin ophthalmic suspension 0.6% may result in overgrowth of non-susceptible organisms, including fungi. If super-infection occurs, discontinue use and institute alternative therapy. Whenever clinical judgment dictates, the patient should be examined with the aid of magnification, such as slit-lamp biomicroscopy, and, where appropriate, fluorescein staining.

5.3 Avoidance of Contact Lenses

Patients should not wear contact lenses if they have signs or symptoms of bacterial conjunctivitis or during the course of therapy with besifloxacin ophthalmic suspension.

6 ADVERSE REACTIONS

Because clinical trials are conducted under widely varying conditions, adverse reaction rates observed in the clinical trials of a drug cannot be directly compared to rates in the clinical trials of another drug and may not reflect the rates observed in clinical practice.

The data described below reflect exposure to besifloxacin ophthalmic suspension in approximately 1,000 patients between 1 and 98 years old with clinical signs and symptoms of bacterial conjunctivitis.

The most frequently reported ocular adverse reaction was conjunctival redness, reported in approximately 2% of patients.

Other adverse reactions reported in patients receiving besifloxacin ophthalmic suspension occurring in approximately 1-2% of patients included: blurred vision, eye pain, eye irritation, eye pruritus and headache.

8 USE IN SPECIFIC POPULATIONS

8.1 Pregnancy

Risk Summary

There are no available human data for the use of besifloxacin ophthalmic suspension during pregnancy to inform any drug-associated risks; however, systemic exposure to besifloxacin from ocular administration is low [see Clinical Pharmacology (12.3)] .

Oral administration of besifloxacin to pregnant rats during organogenesis or during the prenatal and postnatal period did not produce adverse embryofetal or offspring effects at clinically relevant systemic exposures [see Data] .

Data

Animal Data

In an embryofetal development study in rats, the administration of besifloxacin at oral doses up to 1,000 mg/kg/day during organogenesis was not associated with visceral or skeletal malformations in rat fetuses, although this dose was associated with maternal toxicity (reduced body weight gain and food consumption) and maternal mortality. Increased post-implantation loss, decreased fetal body weights, and decreased fetal ossification were also observed. At this dose, the mean Cmaxin the rat dams was approximately 20 mcg/mL, approximately 46,500 times the mean plasma concentrations measured in humans at the recommended human ophthalmic dose (RHOD). The No Observed Adverse Effect Level (NOAEL) for this embryofetal development study was 100 mg/kg/day (Cmax, 5 mcg/mL, approximately 11,600 times the mean plasma concentrations measured in humans at the RHOD).

In a prenatal and postnatal development study in rats, the NOAELs for both fetal/neonate and maternal toxicity were 100 mg/kg/day. At 1,000 mg/kg/day, pups weighed significantly less than controls and had a reduced neonatal survival rate. Attainment of developmental landmarks and sexual maturation was delayed, although surviving pups from this dose group that were reared to maturity did not demonstrate deficits in behavior, including activity, learning and memory, and their reproductive capacity appeared normal.

8.2 Lactation

Risk Summary

There are no data on the presence of besifloxacin ophthalmic suspension in human milk, the effects on the breastfed infant, or the effects on milk production. However, systemic exposure to besifloxacin following topical ocular administration is low [see Clinical Pharmacology (12.3)] , and it is not known whether measurable levels of besifloxacin would be present in maternal milk following topical ocular administration.

The developmental and health benefits of breastfeeding should be considered, along with the mother’s clinical need for besifloxacin ophthalmic suspension, and any potential adverse effects on the breastfed infant from besifloxacin ophthalmic suspension.

8.4 Pediatric Use

The safety and effectiveness of besifloxacin ophthalmic suspension in infants below one year of age have not been established. The efficacy of besifloxacin ophthalmic suspension in treating bacterial conjunctivitis in pediatric patients one year or older has been demonstrated in controlled clinical trials [see Clinical Studies (14)].

There is no evidence that the ophthalmic administration of quinolones has any effect on weight-bearing joints, even though systemic administration of some quinolones has been shown to cause arthropathy in immature animals.

8.5 Geriatric Use

No overall differences in safety and effectiveness have been observed between elderly and younger patients.

11 DESCRIPTION

Besifloxacin ophthalmic suspension 0.6% is a sterile ophthalmic suspension of besifloxacin formulated with DuraSite®†(polycarbophil, edetate disodium dihydrate, sodium chloride, sodium hydroxide, and water for injection). Each mL of besifloxacin ophthalmic suspension contains 6.63 mg besifloxacin hydrochloride equivalent to 6 mg besifloxacin base. It is an 8‑chloro fluoroquinolone anti-infective for topical ophthalmic use.

Chemical Name: (+)-7-[(3R)-3-aminohexahydro-1H-azepin-1-yl]-8-chloro-1-cyclopropyl-6-fluoro-4-oxo-1,4-dihydroquinoline-3-carboxylic acid hydrochloride.

Besifloxacin hydrochloride is a white to pale yellowish-white powder.

Each mL contains:

Active:besifloxacin 0.6% (6 mg/mL);

Inactives:polycarbophil, mannitol, poloxamer 407, sodium chloride, edetate disodium dihydrate, sodium hydroxide, and water for injection.

Preservative:benzalkonium chloride 0.01%

Besifloxacin ophthalmic suspension is an isotonic suspension with an osmolality of approximately 290 mOsm/kg.

12 CLINICAL PHARMACOLOGY

12.1 Mechanism of Action

Besifloxacin is a fluoroquinolone antibacterial [see Microbiology (12.4)] .

12.3 Pharmacokinetics

Plasma concentrations of besifloxacin were measured in adult patients with suspected bacterial conjunctivitis who received besifloxacin ophthalmic suspension bilaterally three times a day (16 doses total). Following the first and last dose, the maximum plasma besifloxacin concentration in each patient was less than 1.3 ng/mL. The mean besifloxacin Cmaxwas 0.37 ng/mL on Day 1 and 0.43 ng/mL on Day 6. The average elimination half-life of besifloxacin in plasma following multiple dosing was estimated to be 7 hours.

12.4 Microbiology

Besifloxacin is an 8-chloro fluoroquinolone with an N-1 cyclopropyl group. The compound has activity against Gram-positive and Gram-negative bacteria due to the inhibition of both bacterial DNA gyrase and topoisomerase IV. DNA gyrase is an essential enzyme required for replication, transcription and repair of bacterial DNA. Topoisomerase IV is an essential enzyme required for partitioning of the chromosomal DNA during bacterial cell division. Besifloxacin is bactericidal with minimum bactericidal concentrations (MBCs) generally within one dilution of the minimum inhibitory concentrations (MICs).

The mechanism of action of fluoroquinolones, including besifloxacin, is different from that of aminoglycoside, macrolide, and β-lactam antibiotics. Therefore, besifloxacin may be active against pathogens that are resistant to these antibiotics and these antibiotics may be active against pathogens that are resistant to besifloxacin. In vitro studies demonstrated cross-resistance between besifloxacin and some fluoroquinolones.

In vitro resistance to besifloxacin develops via multiple-step mutations and occurs at a general frequency of <3.3 x 10^-10for Staphylococcus aureusand <7 x 10^-10for Streptococcus pneumoniae.

Besifloxacin has been shown to be active against most isolates of the following bacteria both in vitro and in conjunctival infections treated in clinical trials [see Indications and Usage (1)] :

1. Aerococcus viridans*
2. CDC coryneform group G
3. Corynebacterium pseudodiphtheriticum*
4. Corynebacterium striatum*
5. Haemophilus influenzae
6. Moraxella catarrhalis*
7. Moraxella lacunata*
8. Pseudomonas aeruginosa*
9. Staphylococcus aureus
10. Staphylococcus epidermidis
11. Staphylococcus hominis*
12. Staphylococcus lugdunensis*
13. Staphylococcus warneri*
14. Streptococcus mitisgroup
15. Streptococcus oralis
16. Streptococcus pneumoniae
17. Streptococcus salivarius*
18. *Efficacy for this organism was studied in fewer than 10 infections.

13 NONCLINICAL TOXICOLOGY

13.1 Carcinogenesis, Mutagenesis, Impairment of Fertility

Long-term studies in animals to determine the carcinogenic potential of besifloxacin have not been performed.

No in vitro mutagenic activity of besifloxacin was observed in an Ames test (up to 3.33 mcg/plate) on bacterial tester strains Salmonella typhimuriumTA98, TA100, TA1535, TA1537 and Escherichia coliWP2uvrA. However, it was mutagenic in S. typhimuriumstrain TA102 and E. colistrain WP2 (pKM101). Positive responses in these strains have been observed with other quinolones and are likely related to topoisomerase inhibition.

Besifloxacin induced chromosomal aberrations in CHO cells in vitro and it was positive in an in vivo mouse micronucleus assay at oral doses ≥1,500 mg/kg. Besifloxacin did not induce unscheduled DNA synthesis in hepatocytes cultured from rats given the test compound up to 2,000 mg/kg by the oral route.

In a fertility and early embryonic development study in rats, besifloxacin did not impair the fertility of male or female rats at oral doses of up to 500 mg/kg/day. This dose is approximately 26,500 times higher than the mean plasma concentration measured in humans at the recommended human ophthalmic dose.

14 CLINICAL STUDIES

In a randomized, double-masked, vehicle-controlled, multicenter clinical trial, in which patients 1-98 years of age were dosed 3 times a day for 5 days, besifloxacin ophthalmic suspension was superior to its vehicle in patients with bacterial conjunctivitis. Clinical resolution was achieved in 45% (90/198) for the besifloxacin ophthalmic suspension-treated group versus 33% (63/191) for the vehicle-treated group (difference 12%, 95% CI 3% - 22%). Microbiological outcomes demonstrated a statistically significant eradication rate for causative pathogens of 91% (181/198) for the besifloxacin ophthalmic suspension-treated group versus 60% (114/191) for the vehicle-treated group (difference 31%, 95% CI 23% - 40%). Microbiologic eradication does not always correlate with clinical outcome in anti-infective trials.

16 HOW SUPPLIED/STORAGE AND HANDLING

Besifloxacin ophthalmic suspension 0.6% is supplied as a sterile ophthalmic suspension in a white low density polyethylene (LDPE) bottle with a controlled dropper tip and beige polypropylene cap. Tamper evidence is provided with a shrink band around the cap and neck area of the package.

NDC 82260-466-05 5 mL in 7.5 mL bottle

Storage:

Store at 15°C to 25°C (59°F to 77°F). Protect from light.

17 PATIENT COUNSELING INFORMATION

Handling the Container

Advise patients to avoid contaminating the applicator tip with material from the eye, fingers or other source.

Use with Contact Lenses

Advise patients not to wear contact lenses if they have signs or symptoms of bacterial conjunctivitis or during the course of therapy with besifloxacin ophthalmic suspension.

Dosing Instructions

Patients should be instructed to invert closed bottle (upside down) and shake once before each use.

Distributed by:

Bausch & Lomb Americas Inc.

Bridgewater, NJ 08807 USA

Manufactured by:

Bausch & Lomb Incorporated

Tampa, FL 33637 USA

Patented. See https://patents.bausch.com for US patent information.

†DuraSite is a trademark of Sun Pharma Global FZE.

© 2022 Bausch & Lomb Incorporated or its affiliates

9781800 (folded)

9781900 (flat)

PACKAGE/LABEL PRINCIPAL DISPLAY PANEL

NDC82260-446-05

Besivance

Ophthalmic

Suspension

0.6%
Sterile

FOR TOPICAL

OPHTHALMIC
USE ONLY

(eye image)

Rx only 5 mL

BAUSCH + LOMB

9781702

MA44507A